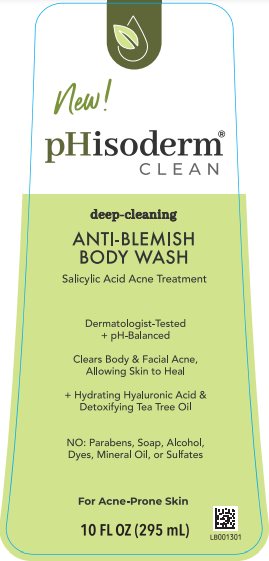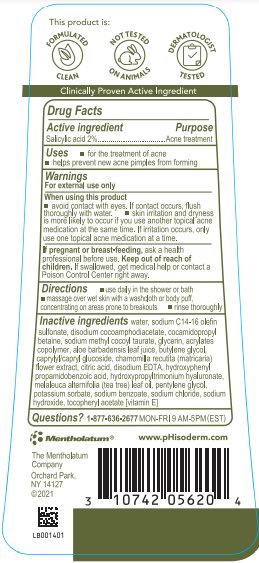 DRUG LABEL: pHisoderm
NDC: 10742-1234 | Form: GEL
Manufacturer: The Mentholatum Company
Category: otc | Type: HUMAN OTC DRUG LABEL
Date: 20241213

ACTIVE INGREDIENTS: SALICYLIC ACID 20 mg/1 mL
INACTIVE INGREDIENTS: WATER; SODIUM C14-16 OLEFIN SULFONATE; DISODIUM COCOAMPHODIACETATE; COCAMIDOPROPYL BETAINE; SODIUM METHYL COCOYL TAURATE; GLYCERIN; BUTYL ACRYLATE/METHYL METHACRYLATE/METHACRYLIC ACID COPOLYMER (18000 MW); ALOE VERA LEAF; BUTYLENE GLYCOL; CAPRYLYL/CAPRYL OLIGOGLUCOSIDE; CHAMOMILE; ANHYDROUS CITRIC ACID; EDETATE DISODIUM; HYDROXYPHENYL PROPAMIDOBENZOIC ACID; DIHYDROXYPROPYLTRIMONIUM; TEA TREE OIL; PENTYLENE GLYCOL; POTASSIUM SORBATE; SODIUM BENZOATE; SODIUM CHLORIDE; SODIUM HYDROXIDE; .ALPHA.-TOCOPHEROL ACETATE

Drug Facts - pHisoderm Clean Anti-Blemish Body Wash

Active ingredient

Salicylic acid 2%

Purpose

Acne treatment

Uses

- for the treatment of acne
- helps prevent new acne pimples from forming

Warnings

For external use only

When using this product

- avoid contact with eyes. If contact occurs, flush thoroughly with water.
- skin irritation and dryness is more likely to occur if you use another topical acne medication at the same time. If irritation occurs, only use one topical acne medication at a time.

If pregnant or breast-feeding,

ask a health professional before use.

Keep out of reach of children.

If swallowed, get medical help or contact a Poison Control Center right away.

Directions

- use daily in the shower or bath
- massage over wet skin with a washcloth or body puff, concentrating on areas prone to breakouts
- rinse thoroughly

Inactive ingredients

water, sodium C14-16 olefin sulfonate, disodium cocoamphodiacetate, cocamidopropyl betaine, sodium methyl cocoyl taurate, glycerin, acrylates copolymer, aloe barbadensis leaf juice, butylene glycol, caprylyl/capryl glucoside, chamomilla recutita (matricaria) flower extract, citric acid, disodium EDTA, hydroxyphenyl propamidobenzoic acid, hydroxypropyltrimonium hyaluronate, melaleuca alternifolia (tea tree) leaf oil, pentylene glycol, potassium sorbate, sodium benzoate, sodium chloride, sodium hydroxide, tocopheryl acetate [vitamin E]

Questions?

1-877-636-2677 MON-FRI 9 AM to 5 PM (EST)